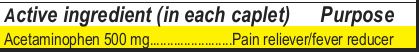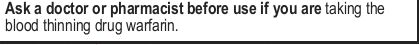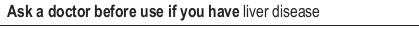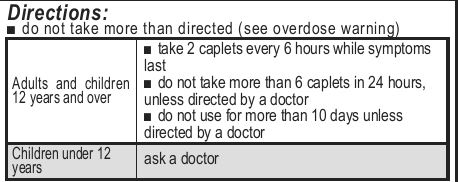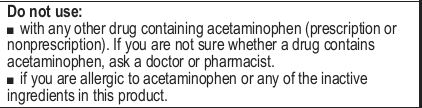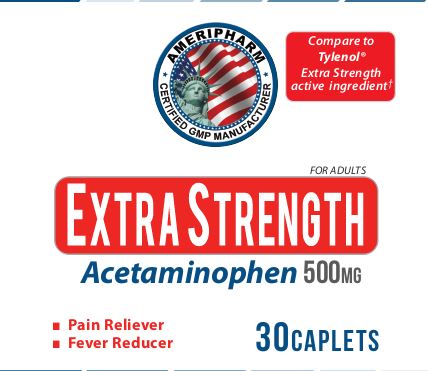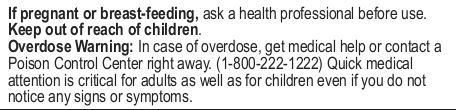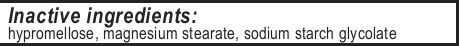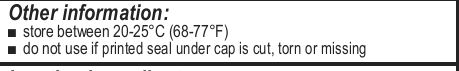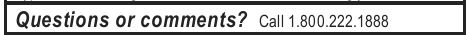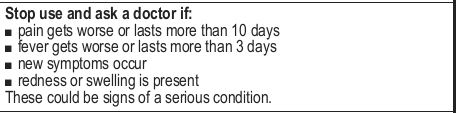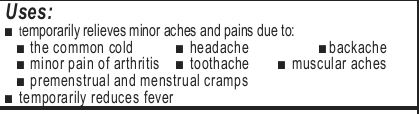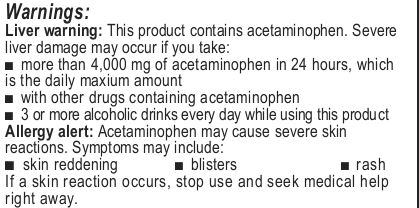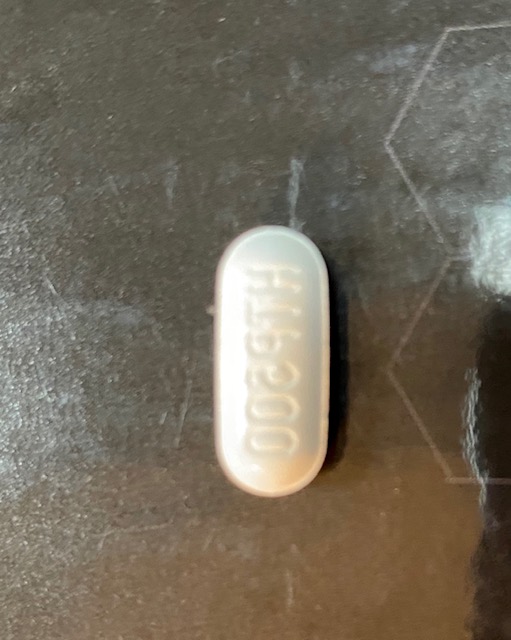 DRUG LABEL: Extra Strength Acetaminophen
NDC: 69732-001 | Form: TABLET
Manufacturer: Hi-Tech Nutraceuticals, LLC
Category: otc | Type: HUMAN OTC DRUG LABEL
Date: 20200420

ACTIVE INGREDIENTS: ACETAMINOPHEN 500 mg/1 1
INACTIVE INGREDIENTS: SODIUM STARCH GLYCOLATE TYPE A POTATO; HYPROMELLOSE, UNSPECIFIED; MAGNESIUM STEARATE

Uses:
■ temporarily relieves minor aches and pains due to:
■ the common cold ■ headache ■backache
■ minor pain of arthritis ■ toothache ■ muscular aches
■ premenstrual and menstrual cramps
■ temporarily reduces fever